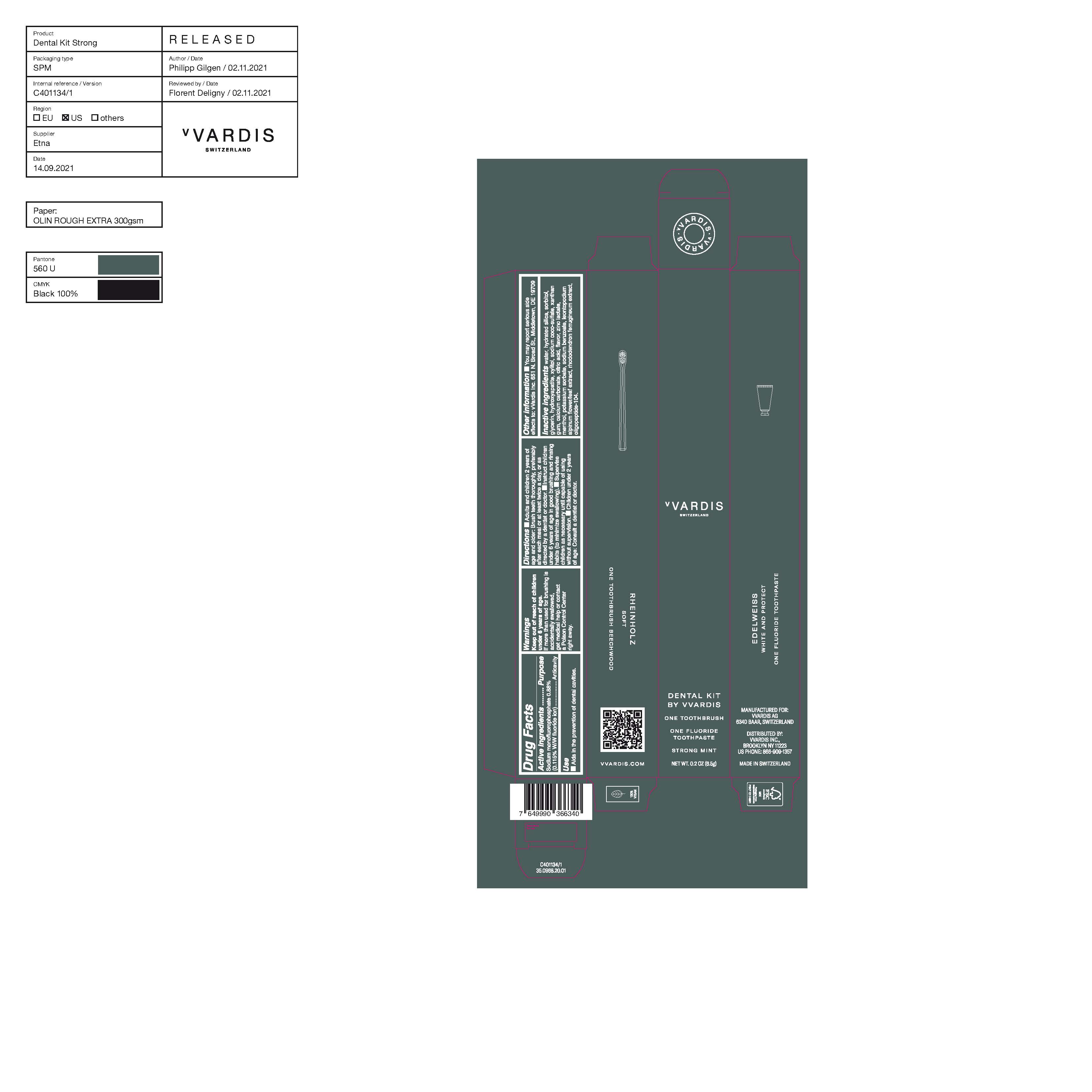 DRUG LABEL: Dental Kit Strong Mint
NDC: 82615-003 | Form: KIT | Route: DENTAL
Manufacturer: vVardis AG
Category: otc | Type: HUMAN OTC DRUG LABEL
Date: 20220304

ACTIVE INGREDIENTS: SODIUM MONOFLUOROPHOSPHATE 0.88 g/100 g
INACTIVE INGREDIENTS: SORBITOL; POTASSIUM SORBATE; RHODODENDRON FERRUGINEUM WHOLE; XYLITOL; WATER; HYDRATED SILICA; GLYCERIN; SODIUM COCO-SULFATE; XANTHAN GUM; CITRIC ACID MONOHYDRATE; MENTHOL, UNSPECIFIED FORM; LEONTOPODIUM ALPINUM FLOWERING TOP; ZINC LACTATE; TRIBASIC CALCIUM PHOSPHATE; CALCIUM CARBONATE

Dental Kit Strong Mint

Active Ingredients Purpose

sodium monofluorophosphate 0.88%

(0.115% W/W fluoride Ion) Anticavity

Use

Aids in the prevention of dental cavities

Keep out of reach of children under 6 years of age.

INDICATIONS AND USAGE

If more than used for brushing is accidentally swallowed, get medical help or contact a poison control center right away.

Keep out of reach of children under 6 years of age.If more than used for brushing is accidentally swallowed, get medical help or contact a Poison Control Center right away.

DOSAGE AND ADMINISTRATION

- Adults and children 2 years of age and older:Brush teeth thoroughly, preferable after each meal or at least twice a day, or as directed by a dentist or doctor.
- Instruct children under 6 years of age in good brushing and rinsing habits (to minimize swallowing)
- Supervise children as necessary until capable of using without supervision
- Children under 2 years of age: consult a dentist or doctor

Inactive Ingredients

water, hydrated silica, sorbitol, glycerin, hydroxyapatite, xylitol, sodium coco-sulfate, xanthan gum, calcium carbonate, citric acid, flavor, zinc lactate, menthol, potassium sorbate, sodium benzoate, leontopodium alpinum flower/leaf extract, rhododendron ferrugineum extract, oligopeptide-104

PACKAGE LABEL

vVARDIS

Switzerland

Dental Kit by VVARDIS

One Toothbrush

One Fluoride toothpaste

Strong Mint

NET. WT. 0.2 OZ (6.5g)